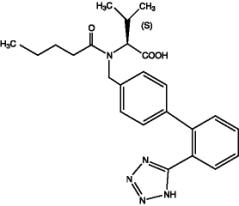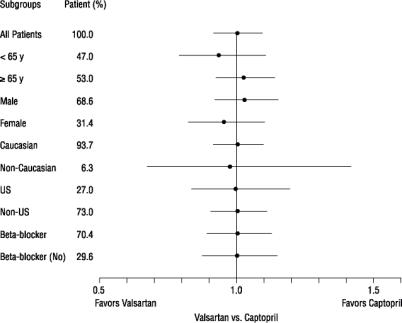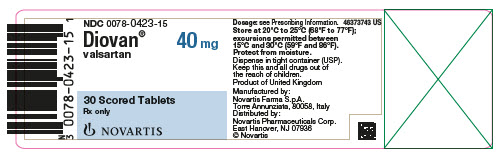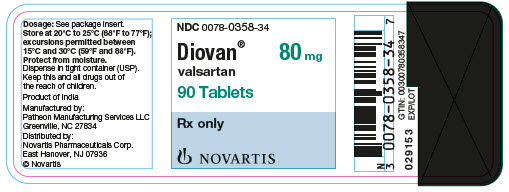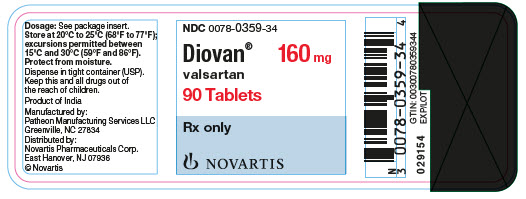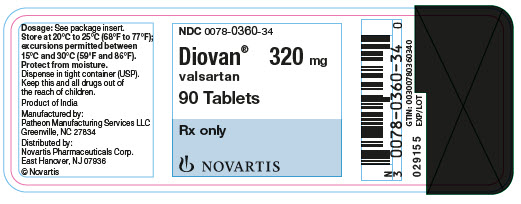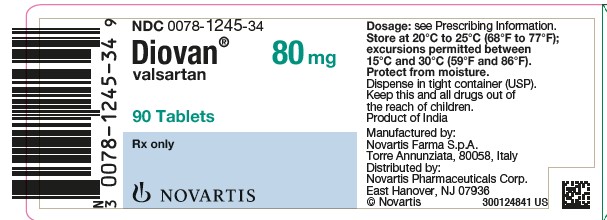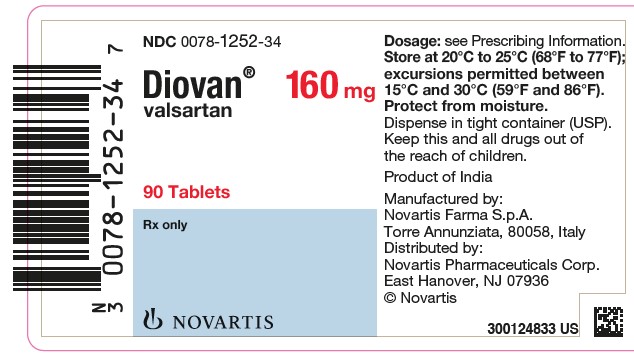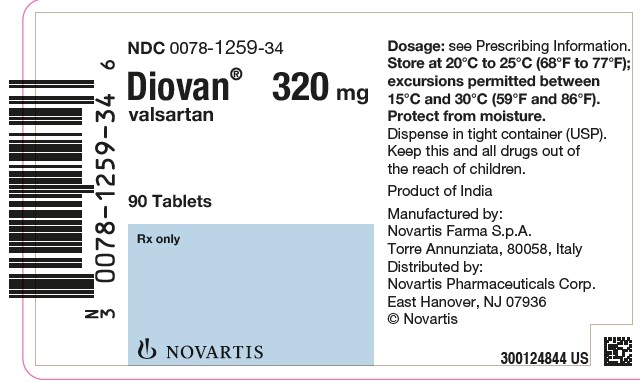 DRUG LABEL: Diovan
NDC: 0078-0423 | Form: TABLET
Manufacturer: Novartis Pharmaceuticals Corporation
Category: prescription | Type: HUMAN PRESCRIPTION DRUG LABEL
Date: 20251222

ACTIVE INGREDIENTS: VALSARTAN 40 mg/1 1
INACTIVE INGREDIENTS: SILICON DIOXIDE; CROSPOVIDONE; HYPROMELLOSES; FERRIC OXIDE YELLOW; MAGNESIUM STEARATE; CELLULOSE, MICROCRYSTALLINE; POLYETHYLENE GLYCOL 8000; TITANIUM DIOXIDE

HIGHLIGHTS OF PRESCRIBING INFORMATION

These highlights do not include all the information needed to use DIOVAN safely and effectively. See full prescribing information for DIOVAN.
DIOVAN® (valsartan) tablets, for oral use
Initial U.S. Approval: 1996

WARNING: FETAL TOXICITY

See full prescribing information for complete boxed warning.

- When pregnancy is detected, discontinue Diovan as soon as possible. (5.1)
- Drugs that act directly on the renin-angiotensin system can cause injury and death to the developing fetus. (5.1)

1 INDICATIONS AND USAGE

Diovan is an angiotensin II receptor blocker (ARB) indicated for:

- Hypertension, to lower blood pressure in adults and children 1 year and older. Lowering blood pressure reduces the risk of fatal and nonfatal cardiovascular events, primarily strokes and myocardial infarctions (1.1)
- Heart failure (NYHA class II-IV), to reduce hospitalization for heart failure in adults (1.2)
- Post-myocardial infarction, for the reduction of cardiovascular mortality in clinically stable patients with left ventricular failure or left ventricular dysfunction following myocardial infarction in adults (1.3)

2 DOSAGE AND ADMINISTRATION

Indication | Starting Dose | Dose Range*
Hypertension Adults (2.2) | 80 mg to 160 mg once daily | 80 mg to 320 mg once daily
1 to 16 years (2.3) | 1 mg/kg once daily Up to 40 mg daily | 1 mg/kg to 4 mg/kg once daily Up to 160 mg daily
Heart Failure (2.4) | 40 mg twice daily | 40 mg to 160 mg twice daily
Post-Myocardial Infarction (2.5) | 20 mg twice daily | 20 mg to 160 mg twice daily
*As tolerated by patient

3 DOSAGE FORMS AND STRENGTHS

Tablets: 40 mg (functional score), 80 mg, 160 mg, 320 mg

4 CONTRAINDICATIONS

Known hypersensitivity to any component.

Do not coadminister aliskiren with Diovan in patients with diabetes (4)

5 WARNINGS AND PRECAUTIONS

- Observe for signs and symptoms of hypotension (5.2)
- Monitor renal function and potassium in susceptible patients (5.3, 5.4)

6 ADVERSE REACTIONS

Hypertension: Most common adverse reactions are headache, dizziness, viral infection, fatigue and abdominal pain (6.1)

Heart Failure: Most common adverse reactions are dizziness, hypotension, diarrhea, arthralgia, back pain, fatigue and hyperkalemia (6.1)

Post-Myocardial Infarction: Most common adverse reactions which caused patients to discontinue therapy are hypotension, cough and increased blood creatinine (6.1)

To report SUSPECTED ADVERSE REACTIONS, contact Novartis Pharmaceuticals Corporation at 1-888-669-6682 or FDA at 1-800-FDA-1088 or www.fda.gov/medwatch.

7 DRUG INTERACTIONS

- Potassium-sparing diuretics, potassium supplements or salt substitutes may lead to increases in serum potassium, and in heart failure patients, increases in serum creatinine (7.1)
- Non-Steroidal Anti-Inflammatory Drug (NSAID) use may lead to increased risk of renal impairment and loss of antihypertensive effect (7.2)
- Dual inhibition of the Renin-Angiotensin System (RAS): Increased risk of renal impairment, hypotension, and hyperkalemia (7.3)
- Lithium: Increases in serum lithium level and lithium toxicity (7.4)

8 USE IN SPECIFIC POPULATIONS

Lactation: Breastfeeding is not recommended (8.2)

Pediatrics: Use of Diovan is not recommended in children less than 1 year of age (6.1, 8.4, 13.2)

FULL PRESCRIBING INFORMATION

WARNING: FETAL TOXICITY

- When pregnancy is detected, discontinue Diovan as soon as possible. (5.1)
- Drugs that act directly on the renin-angiotensin system can cause injury and death to the developing fetus. (5.1)

1 INDICATIONS AND USAGE

1.1 Hypertension

Diovan® is indicated for the treatment of hypertension, to lower blood pressure in adults and pediatric patients one year of age and older. Lowering blood pressure reduces the risk of fatal and nonfatal cardiovascular events, primarily strokes and myocardial infarctions. These benefits have been seen in controlled trials of antihypertensive drugs from a wide variety of pharmacologic classes, including the class to which valsartan principally belongs. There are no controlled trials in hypertensive patients demonstrating risk reduction with Diovan.

Control of high blood pressure should be part of comprehensive cardiovascular risk management, including, as appropriate, lipid control, diabetes management, antithrombotic therapy, smoking cessation, exercise, and limited sodium intake. Many patients will require more than one drug to achieve blood pressure goals. For specific advice on goals and management, see published guidelines, such as those of the National High Blood Pressure Education Program’s Joint National Committee on Prevention, Detection, Evaluation, and Treatment of High Blood Pressure (JNC).

Numerous antihypertensive drugs, from a variety of pharmacologic classes and with different mechanisms of action, have been shown in randomized controlled trials to reduce cardiovascular morbidity and mortality, and it can be concluded that it is blood pressure reduction, and not some other pharmacologic property of the drugs, that is largely responsible for those benefits. The largest and most consistent cardiovascular outcome benefit has been a reduction in the risk of stroke, but reductions in myocardial infarction and cardiovascular mortality also have been seen regularly.

Elevated systolic or diastolic pressure causes increased cardiovascular risk, and the absolute risk increase per mmHg is greater at higher blood pressures, so that even modest reductions of severe hypertension can provide substantial benefit. Relative risk reduction from blood pressure reduction is similar across populations with varying absolute risk, so the absolute benefit is greater in patients who are at higher risk independent of their hypertension (e.g., patients with diabetes or hyperlipidemia), and such patients would be expected to benefit from more aggressive treatment to a lower blood pressure goal.

Some antihypertensive drugs have smaller blood pressure effects (as monotherapy) in black patients, and many antihypertensive drugs have additional approved indications and effects (e.g., on angina, heart failure, or diabetic kidney disease). These considerations may guide selection of therapy.

Diovan may be used alone or in combination with other antihypertensive agents.

1.2 Heart Failure

Diovan is indicated to reduce the risk of hospitalization for heart failure in adult patients with heart failure (NYHA class II-IV). There is no evidence that Diovan provides added benefits when it is used with an adequate dose of an angiotensin converting enzyme (ACE) inhibitor [see Clinical Studies (14.2)].

1.3 Post-Myocardial Infarction

In clinically stable adult patients with left ventricular failure or left ventricular dysfunction following myocardial infarction, Diovan is indicated to reduce the risk of cardiovascular mortality [see Clinical Studies (14.3)].

2 DOSAGE AND ADMINISTRATION

2.1 Important Dosage and Preparation Information

Diovan tablets and oral suspension are not substitutable on a milligram-per-milligram basis. Do not combine two dosage forms to achieve the total dose. The systemic exposure to valsartan (AUC) is 60% higher with the suspension compared to tablets [see Clinical Pharmacology (12.3)].

Use of the oral suspension is recommended:

- in pediatric patients aged 1 to 5 years
- in patients >5 years of age who cannot swallow tablets and
- in pediatric patients for whom the calculated dose (mg/kg) does not correspond to the available tablet strengths of Diovan.

When switching between suspension and tablets, the dose of valsartan may need to be adjusted.

Preparation of Suspension (for 160 mL of a 4 mg/mL suspension)

- Add 80 mL of Ora-Plus®* oral suspending vehicle to an amber glass bottle containing 8 Diovan 80 mg tablets and shake for a minimum of 2 minutes.
- Allow the suspension to stand for a minimum of 1 hour.
- After the standing time, shake the suspension for a minimum of 1 additional minute.
- Add 80 mL of Ora-Sweet SF®* oral sweetening vehicle to the bottle and shake the suspension for at least 10 seconds to disperse the ingredients.
- The suspension is homogenous and can be stored for either up to 30 days at room temperature (below 30°C/86°F) or up to 75 days at refrigerated conditions (2°C to 8°C/35°F to 46°F) in the glass bottle with a child-resistant screw-cap closure.
- Shake the bottle well (at least 10 seconds) prior to dispensing the suspension.

*Ora-Sweet SF® and Ora-Plus® are registered trademarks of Paddock Laboratories, Inc.

2.2 Adult Hypertension

The recommended starting dose of Diovan is 80 mg or 160 mg once daily when used as monotherapy in patients who are not volume-depleted. Patients requiring greater reductions may be started at the higher dose. Diovan may be used over a dose range of 80 mg to 320 mg daily, administered once a day.

The antihypertensive effect is substantially present within 2 weeks and maximal reduction is generally attained after 4 weeks. If additional antihypertensive effect is required over the starting dose range, the dose may be increased to a maximum of 320 mg or a diuretic may be added. Addition of a diuretic has a greater effect than dose increases beyond 80 mg.

Diovan may be administered with other antihypertensive agents.

2.3 Pediatric Hypertension 1 to 16 Years of Age

The usual recommended starting dose is 1 mg/kg once daily (up to 40 mg total). A higher starting dose of 2 mg/kg may be considered in selected cases when a greater reduction of blood pressure is needed. The dosage should be adjusted according to blood pressure response and tolerability, up to a maximum dose of 4 mg/kg once daily (maximum daily dose 160 mg).

No data are available in pediatric patients either undergoing dialysis or with a glomerular filtration rate < 30 mL/min/1.73 m^2 [see Use in Specific Populations (8.4)].

Use of Diovan is not recommended in children less than 1 year of age [see Adverse Reactions (6.1), Pediatric Use in Specific Populations (8.4), Nonclinical Toxicology (13.2)].

2.4 Heart Failure

The recommended starting dose of Diovan is 40 mg twice daily. Uptitrate to 80 mg and 160 mg twice daily or to the highest dose tolerated by the patient. Consider reducing the dose of concomitant diuretics. The maximum daily dose administered in clinical trials is 320 mg in divided doses.

2.5 Post-Myocardial Infarction

Diovan may be initiated as early as 12 hours after a myocardial infarction. The recommended starting dose of Diovan is 20 mg twice daily. Patients may be uptitrated within 7 days to 40 mg twice daily, with subsequent titrations to a target maintenance dose of 160 mg twice daily, as tolerated by the patient. If symptomatic hypotension or renal dysfunction occurs, consider dosage reduction. Diovan may be given with other standard post-myocardial infarction treatment, including thrombolytics, aspirin, beta-blockers, and statins.

2.6 Missed Dose

If a dose of DIOVAN is missed, it should be administered as soon as possible, unless it is almost time for the next dose. The dose should not be doubled to make up for a missed dose.

3 DOSAGE FORMS AND STRENGTHS

40 mg are functionally scored yellow ovaloid tablets with beveled edges, imprinted NVR/DO (Side 1/Side 2)

40 mg are yellow, ovaloid film-coated tablets with beveled edges, slightly convex, functionally scored on one side, with debossing “D” on one side and “O” on the other side of the score and “NVR” on the reverse side of the tablet

80 mg are pale red almond-shaped tablets with beveled edges, imprinted NVR/DV

80 mg are pale red round film-coated tablets with beveled edges, scored on one side with debossing “D” on one side and “V” on the other side of the score and “NVR” on the reverse side of the tablet

160 mg are grey-orange almond-shaped tablets with beveled edges, imprinted NVR/DX

160 mg are grey-orange ovaloid film-coated tablets, slightly convex, scored on one side with debossing “DX” on one side of the score and “DX” on the other side of the score “NVR” on the reverse side of the tablet

320 mg are dark grey-violet almond-shaped tablets with beveled edges, imprinted NVR/DXL

320 mg are dark grey-violet ovaloid film-coated tablets with beveled edges, slightly convex, scored on one side with debossing “DC” on one side of the score and “DC” on the other side of the score and “NVR” on the reverse side of the tablet

4 CONTRAINDICATIONS

Do not use in patients with known hypersensitivity to any component.

Do not coadminister aliskiren with Diovan in patients with diabetes [see Drug Interactions (7.3)].

5 WARNINGS AND PRECAUTIONS

5.1 Fetal Toxicity

Diovan can cause fetal harm when administered to a pregnant woman. Use of drugs that act on the renin-angiotensin system during the second and third trimesters of pregnancy reduces fetal renal function and increases fetal and neonatal morbidity and death. Resulting oligohydramnios can be associated with fetal lung hypoplasia and skeletal deformations. Potential neonatal adverse effects include skull hypoplasia, anuria, hypotension, renal failure, and death. When pregnancy is detected, discontinue Diovan as soon as possible [see Use in Specific Populations (8.1)].

5.2 Hypotension

Excessive hypotension was rarely seen (0.1%) in patients with uncomplicated hypertension treated with Diovan alone. In patients with an activated renin-angiotensin system, such as volume- and/or salt-depleted patients receiving high doses of diuretics, symptomatic hypotension may occur. This condition should be corrected prior to administration of Diovan, or the treatment should start under close medical supervision.

Patients with heart failure or post-myocardial infarction patients given Diovan commonly have some reduction in blood pressure, but discontinuation of therapy because of continuing symptomatic hypotension usually is not necessary when dosing instructions are followed. In controlled trials in heart failure patients, the incidence of hypotension in valsartan-treated patients was 5.5% compared to 1.8% in placebo-treated patients. In the VALsartan In Acute myocardial iNfarcTion trial (VALIANT), hypotension in post-myocardial infarction patients led to permanent discontinuation of therapy in 1.4% of valsartan-treated patients and 0.8% of captopril-treated patients.

If excessive hypotension occurs, place the patient in the supine position and, if necessary, give intravenous normal saline. A transient hypotensive response is not a contraindication to further treatment, which usually can be continued without difficulty once the blood pressure has stabilized.

5.3 Impaired Renal Function

Changes in renal function including acute renal failure can be caused by drugs that inhibit the renin-angiotensin system and by diuretics. Patients whose renal function may depend in part on the activity of the renin-angiotensin system (e.g., patients with renal artery stenosis, chronic kidney disease, severe congestive heart failure, or volume depletion) may be at particular risk of developing acute renal failure on Diovan. Monitor renal function periodically in these patients. Consider withholding or discontinuing therapy in patients who develop a clinically significant decrease in renal function on Diovan [see Drug Interactions (7)].

5.4 Hyperkalemia

Some patients with heart failure have developed increases in potassium. These effects are usually minor and transient, and they are more likely to occur in patients with pre-existing renal impairment. Dosage reduction and/or discontinuation of Diovan may be required [see Adverse Reactions (6.1)].

6 ADVERSE REACTIONS

6.1 Clinical Trials Experience

Because clinical studies are conducted under widely varying conditions, adverse reaction rates observed in the clinical studies of a drug cannot be directly compared to rates in the clinical studies of another drug and may not reflect the rates observed in practice.

Adult Hypertension

Diovan has been evaluated for safety in more than 4000 patients, including over 400 treated for over 6 months, and more than 160 for over 1 year. Adverse reactions have generally been mild and transient in nature and have only infrequently required discontinuation of therapy. The overall incidence of adverse reactions with Diovan was similar to placebo.

The overall frequency of adverse reactions was neither dose-related nor related to gender, age, race, or regimen. Discontinuation of therapy due to side effects was required in 2.3% of valsartan patients and 2.0% of placebo patients. The most common reasons for discontinuation of therapy with Diovan were headache and dizziness.

The adverse reactions that occurred in placebo-controlled clinical trials in at least 1% of patients treated with Diovan and at a higher incidence in valsartan (n = 2316) than placebo (n = 888) patients included viral infection (3% vs. 2%), fatigue (2% vs. 1%), and abdominal pain (2% vs. 1%).

In trials in which valsartan was compared to an ACE inhibitor with or without placebo, the incidence of dry cough was significantly greater in the ACE-inhibitor group (7.9%) than in the groups who received valsartan (2.6%) or placebo (1.5%). In a 129-patient trial limited to patients who had had dry cough when they had previously received ACE inhibitors, the incidences of cough in patients who received valsartan, HCTZ, or lisinopril were 20%, 19%, and 69% respectively (p < 0.001).

Dose-related orthostatic effects were seen in less than 1% of patients. An increase in the incidence of dizziness was observed in patients treated with Diovan 320 mg (8%) compared to 10 mg to 160 mg (2% to 4%).

Pediatric Hypertension

Diovan has been evaluated for safety in 290 pediatric patients aged 1 to less than 6 years and over 400 patients aged 6 to 17 years. No relevant differences were identified between the adverse experience profile for pediatric patients and that previously reported for adult patients. Hyperkalemia was more frequently observed in pediatric patients aged 1 to 17 years with underlying chronic kidney disease (CKD).

Cases of elevated ALT and/or AST have been reported in pediatric patients 1 to less than 6 years of age. These events occurred in a study population which frequently had significant comorbidities; hence, a causal relationship to valsartan could not be established.

Heart Failure

In the Valsartan Heart Failure Trial (Val-HeFT), comparing valsartan in total daily doses up to 320 mg (n = 2506) to placebo (n = 2494), 10% of valsartan patients discontinued for adverse reactions vs. 7% of placebo patients.

The table shows adverse reactions in double-blind short-term heart failure trials, including the first 4 months of the Valsartan Heart Failure Trial, with an incidence of at least 2% that were more frequent in valsartan-treated patients than in placebo-treated patients. All patients received standard drug therapy for heart failure, frequently as multiple medications, which could include diuretics, digitalis, beta-blockers. About 93% of patients received concomitant ACE inhibitors.

 | Valsartan (n = 3282) | Placebo (n = 2740)
Dizziness | 17% | 9%
Hypotension | 7% | 2%
Diarrhea | 5% | 4%
Arthralgia | 3% | 2%
Fatigue | 3% | 2%
Back Pain | 3% | 2%
Dizziness, postural | 2% | 1%
Hyperkalemia | 2% | 1%
Hypotension, postural | 2% | 1%

Discontinuations occurred in 0.5% of valsartan-treated patients and 0.1% of placebo patients for each of the following: elevations in creatinine and elevations in potassium.

Other adverse reactions with an incidence greater than 1% and greater than placebo included headache, nausea, renal impairment, syncope, blurred vision, upper abdominal pain and vertigo.

From the long-term data in the Valsartan Heart Failure Trial, there did not appear to be any significant adverse reactions not previously identified.

Post-Myocardial Infarction

The table shows the percentage of patients discontinued in the valsartan and captopril-treated groups in the VALsartan In Acute myocardial iNfarcTion trial (VALIANT) with a rate of at least 0.5% in either of the treatment groups.

Discontinuations due to renal dysfunction occurred in 1.1% of valsartan-treated patients and 0.8% of captopril-treated patients.

 | Valsartan (n = 4885) | Captopril (n = 4879)
Discontinuation for adverse reaction | 5.8% | 7.7%
Adverse reactions
Hypotension NOS | 1.4% | 0.8%
Cough | 0.6% | 2.5%
Blood creatinine increased | 0.6% | 0.4%
Rash NOS | 0.2% | 0.6%

Clinical Laboratory Test Findings

Creatinine: In heart failure trials, greater than 50% increases in creatinine were observed in 3.9% of Diovan-treated patients compared to 0.9% of placebo-treated patients. In post-myocardial infarction patients, doubling of serum creatinine was observed in 4.2% of valsartan-treated patients and 3.4% of captopril-treated patients.

Neutropenia: Neutropenia was observed in 1.9% of patients treated with Diovan and 0.8% of patients treated with placebo.

Blood Urea Nitrogen (BUN): In heart failure trials, greater than 50% increases in BUN were observed in 16.6% of Diovan-treated patients compared to 6.3% of placebo-treated patients [see Warnings and Precautions (5.3)].

6.2 Postmarketing Experience

The following additional adverse reactions have been reported in postmarketing use of Diovan. Because these reactions are reported voluntarily from a population of uncertain size, it is not always possible to reliably estimate their frequency or establish a causal relationship to drug exposure.

Hypersensitivity: Angioedema has been reported. Some of these patients previously experienced angioedema with other drugs, including ACE inhibitors. Diovan should not be re-administered to patients who have had angioedema.

Digestive: Elevated liver enzymes and very rare reports of hepatitis

Musculoskeletal: Rhabdomyolysis

Renal: Impaired renal function, renal failure

Dermatologic: Alopecia, bullous dermatitis

Blood and Lymphatic: Thrombocytopenia

Vascular: Vasculitis

7 DRUG INTERACTIONS

7.1 Agents Increasing Serum Potassium

Concomitant use of valsartan with other agents that block the renin-angiotensin system, potassium-sparing diuretics (e.g., spironolactone, triamterene, amiloride), potassium supplements, salt substitutes containing potassium or other drugs that may increase potassium levels (e.g., heparin) may lead to increases in serum potassium and in heart failure patients to increases in serum creatinine. If co-medication is considered necessary, monitoring of serum potassium is advisable.

7.2 Non-Steroidal Anti-Inflammatory Agents Including Selective Cyclooxygenase-2 Inhibitors (COX-2 Inhibitors)

In patients who are elderly, volume-depleted (including those on diuretic therapy), or with compromised renal function, coadministration of NSAIDs, including selective COX-2 inhibitors, with angiotensin II receptor antagonists, including valsartan, may result in deterioration of renal function, including possible acute renal failure. These effects are usually reversible. Monitor renal function periodically in patients receiving valsartan and NSAID therapy.

The antihypertensive effect of angiotensin II receptor antagonists, including valsartan, may be attenuated by NSAIDs, including selective COX-2 inhibitors.

7.3 Dual Blockade of the Renin-Angiotensin System (RAS)

Dual blockade of the RAS with angiotensin receptor blockers, ACE inhibitors, or aliskiren is associated with increased risks of hypotension, hyperkalemia, and changes in renal function (including acute renal failure) compared to monotherapy. Most patients receiving the combination of two RAS inhibitors do not obtain any additional benefit compared to monotherapy [see Clinical Studies (14.3)]. In general, avoid combined use of RAS inhibitors. Closely monitor blood pressure, renal function and electrolytes in patients on Diovan and other agents that affect the RAS.

Do not coadminister aliskiren with Diovan in patients with diabetes. Avoid use of aliskiren with Diovan in patients with renal impairment (GFR < 60 mL/min).

7.4 Lithium

Increases in serum lithium concentrations and lithium toxicity have been reported during concomitant administration of lithium with angiotensin II receptor antagonists. Monitor serum lithium levels during concomitant use.

8 USE IN SPECIFIC POPULATIONS

8.1 Pregnancy

Risk Summary

Diovan can cause fetal harm when administered to a pregnant woman. Use of drugs that act on the renin-angiotensin system during the second and third trimesters of pregnancy reduces fetal renal function and increases fetal and neonatal morbidity and death. Most epidemiologic studies examining fetal abnormalities after exposure to antihypertensive use in the first trimester have not distinguished drugs affecting the renin-angiotensin system from other antihypertensive agents. Published reports include cases of anhydramnios and oligohydramnios in pregnant women treated with valsartan (see Clinical Considerations).

When pregnancy is detected, consider alternative drug treatment and discontinue Diovan as soon as possible.

The estimated background risk of major birth defects and miscarriage for the indicated population is unknown. All pregnancies have a background risk of birth defect, loss, or other adverse outcomes. In the U.S. general population, the estimated background risk of major birth defects and miscarriage in clinically recognized pregnancies is 2% to 4% and 15% to 20%, respectively.

Clinical Considerations

Disease-associated maternal and/or embryo/fetal risk

Hypertension in pregnancy increases the maternal risk for pre-eclampsia, gestational diabetes, premature delivery, and delivery complications (e.g., need for cesarean section, and post-partum hemorrhage). Hypertension increases the fetal risk for intrauterine growth restriction and intrauterine death. Pregnant women with hypertension should be carefully monitored and managed accordingly.

Fetal/Neonatal Adverse Reactions

Oligohydramnios in pregnant women who use drugs affecting the renin-angiotensin system in the second and third trimesters of pregnancy can result in the following: reduced fetal renal function leading to anuria and renal failure, fetal lung hypoplasia, skeletal deformations, including skull hypoplasia, hypotension and death. In the unusual case that there is no appropriate alternative to therapy with drugs affecting the renin-angiotensin system for a particular patient, apprise the mother of the potential risk to the fetus.

In patients taking Diovan during pregnancy, perform serial ultrasound examinations to assess the intra-amniotic environment. Fetal testing may be appropriate, based on the week of gestation. Patients and physicians should be aware, however, that oligohydramnios may not appear until after the fetus has sustained irreversible injury. If oligohydramnios is observed, consider alternative drug treatment. Closely observe neonates with histories of in utero exposure to Diovan for hypotension, oliguria, and hyperkalemia. In neonates with a history of in utero exposure to Diovan, if oliguria or hypotension occurs, support blood pressure and renal perfusion. Exchange transfusions or dialysis may be required as a means of reversing hypotension and replacing renal function.

Data

Animal Data

No teratogenic effects were observed when valsartan was administered to pregnant mice and rats at oral doses of up to 600 mg/kg/day (9 and 18 times the maximum recommended human dose (MRHD) on a mg/m^2 basis) and to pregnant rabbits at oral doses of up to 10 mg/kg/day.

In rats, oral valsartan administered at maternally toxic doses (600 mg/kg/day) during organogenesis or late gestation and lactation, resulted in decreased fetal and pup weight, pup survival and delayed developmental milestones. In rabbits administered maternally toxic doses of 5 mg/kg/day and 10 mg/kg/day, fetotoxicity was observed.

8.2 Lactation

Risk Summary

There is no information regarding the presence of Diovan in human milk, the effects on the breastfed infant, or the effects on milk production. Diovan is present in rat milk. Because of the potential for serious adverse reactions in breastfed infants from exposure to valsartan, advise a nursing woman that breastfeeding is not recommended during treatment with Diovan.

Data

Valsartan was detected in the milk of lactating rats 15 minutes after oral administration of a 3 mg/kg dose.

8.4 Pediatric Use

The antihypertensive effects of Diovan have been evaluated in 5 clinical studies in pediatric patients from 1-16 years of age [see Clinical Studies (14.1)]. The pharmacokinetics of Diovan have been evaluated in pediatric patients 1 to 16 years of age [see Clinical Pharmacology (12.3)]. The adverse experience profile of Diovan was similar to that described for adults [see Adverse Reactions (6.1)].

In children and adolescents with hypertension where underlying renal abnormalities may be more common, renal function and serum potassium should be closely monitored as clinically indicated.

Use of Diovan is not recommended in children less than 1 year of age [see Nonclinical Toxicology (13.2)]. It is not known whether post-natal use of valsartan, before maturation of renal function is complete, has a long-term deleterious effect on the kidney.

No data are available in pediatric patients either undergoing dialysis or with a glomerular filtration rate less than 30 mL/min/1.73 m^2.

8.5 Geriatric Use

In the controlled clinical trials of valsartan, 1214 (36.2%) hypertensive patients treated with valsartan were ≥ 65 years and 265 (7.9%) were ≥ 75 years. No overall difference in the efficacy or safety of valsartan was observed in this patient population, but greater sensitivity of some older individuals cannot be ruled out. Exposure [measured by area under the curve (AUC)] to valsartan is higher by 70% in the elderly than in the young, however no dosage adjustment is necessary [see Clinical Pharmacology (12.3)].

Of the 2511 patients with heart failure randomized to valsartan in the Valsartan Heart Failure Trial, 45% (1,141) were 65 years of age or older. In the VALsartan In Acute myocardial iNfarcTion trial (VALIANT), 53% (2596) of the 4909 patients treated with valsartan and 51% (2515) of the 4885 patients treated with valsartan + captopril were 65 years of age or older. There were no notable differences in efficacy or safety between older and younger patients in either trial.

8.6 Renal Impairment

Safety and effectiveness of Diovan in patients with severe renal impairment (glomerular filtration rate less than 30 mL/min/1.73 m^2) have not been established. No dose adjustment is required in patients with mild (glomerular filtration rate 60 to 90 mL/min/1.73 m^2) or moderate (glomerular filtration rate 30 to 60 mL/min/1.73 m^2) renal impairment.

8.7 Hepatic Impairment

No dose adjustment is necessary for patients with mild-to-moderate liver disease. No dosing recommendations can be provided for patients with severe liver disease.

10 OVERDOSAGE

Limited data are available related to overdosage in humans. The most likely manifestations of overdosage would be hypotension and tachycardia; bradycardia could occur from parasympathetic (vagal) stimulation. Depressed level of consciousness, circulatory collapse and shock have been reported. If symptomatic hypotension should occur, institute supportive treatment.

Diovan (valsartan) is not removed from the plasma by hemodialysis.

Valsartan was without grossly observable adverse effects at single oral doses up to 2000 mg/kg in rats and up to 1000 mg/kg in marmosets, except for salivation and diarrhea in the rat and vomiting in the marmoset at the highest dose (60 and 31 times, respectively, the MRHD dose on a mg/m^2 basis) (Calculations assume an oral dose of 320 mg/day and a 60-kg patient).

11 DESCRIPTION

Diovan (valsartan) is a nonpeptide, orally active, and specific angiotensin II receptor blocker acting on the AT1 receptor subtype.

Valsartan is chemically described as N-(1-oxopentyl)-N-[[2′-(1H-tetrazol-5-yl) [1,1′-biphenyl]-4-yl]methyl]-L-valine. Its empirical formula is C24H29N5O3, its molecular weight is 435.5, and its structural formula is:

Valsartan is a white to practically white fine powder. It is soluble in ethanol and methanol and slightly soluble in water.

Diovan is available as tablets for oral administration, containing 40 mg, 80 mg, 160 mg or 320 mg of valsartan. The inactive ingredients of the tablets are colloidal silicon dioxide, crospovidone, hydroxypropyl methylcellulose, iron oxides (yellow, black and/or red), magnesium stearate, microcrystalline cellulose, polyethylene glycol 8000, and titanium dioxide.

12 CLINICAL PHARMACOLOGY

12.1 Mechanism of Action

Angiotensin II is formed from angiotensin I in a reaction catalyzed by angiotensin-converting enzyme (ACE, kininase II). Angiotensin II is the principal pressor agent of the renin-angiotensin system, with effects that include vasoconstriction, stimulation of synthesis and release of aldosterone, cardiac stimulation, and renal reabsorption of sodium. Diovan (valsartan) blocks the vasoconstrictor and aldosterone-secreting effects of angiotensin II by selectively blocking the binding of angiotensin II to the AT1 receptor in many tissues, such as vascular smooth muscle and the adrenal gland. Its action is therefore independent of the pathways for angiotensin II synthesis.

There is also an AT2 receptor found in many tissues, but AT2 is not known to be associated with cardiovascular homeostasis. Valsartan has much greater affinity (about 20,000-fold) for the AT1 receptor than for the AT2 receptor. The increased plasma levels of angiotensin II following AT1 receptor blockade with valsartan may stimulate the unblocked AT2 receptor. The primary metabolite of valsartan is essentially inactive with an affinity for the AT1 receptor about one-200th (1/200th) that of valsartan itself.

Blockade of the renin-angiotensin system with ACE inhibitors, which inhibit the biosynthesis of angiotensin II from angiotensin I, is widely used in the treatment of hypertension. ACE inhibitors also inhibit the degradation of bradykinin, a reaction also catalyzed by ACE. Because valsartan does not inhibit ACE (kininase II), it does not affect the response to bradykinin. Whether this difference has clinical relevance is not yet known. Valsartan does not bind to or block other hormone receptors or ion channels known to be important in cardiovascular regulation.

Blockade of the angiotensin II receptor inhibits the negative regulatory feedback of angiotensin II on renin secretion, but the resulting increased plasma renin activity and angiotensin II circulating levels do not overcome the effect of valsartan on blood pressure.

12.2 Pharmacodynamics

Valsartan inhibits the pressor effect of angiotensin II infusions. An oral dose of 80 mg inhibits the pressor effect by about 80% at peak with approximately 30% inhibition persisting for 24 hours. No information on the effect of larger doses is available.

Removal of the negative feedback of angiotensin II causes a 2- to 3-fold rise in plasma renin and consequent rise in angiotensin II plasma concentration in hypertensive patients. Minimal decreases in plasma aldosterone were observed after administration of valsartan; very little effect on serum potassium was observed.

In multiple-dose studies in hypertensive patients with stable renal insufficiency and patients with renovascular hypertension, valsartan had no clinically significant effects on glomerular filtration rate, filtration fraction, creatinine clearance, or renal plasma flow.

In multiple-dose studies in hypertensive patients, valsartan had no notable effects on total cholesterol, fasting triglycerides, fasting serum glucose, or uric acid.

12.3 Pharmacokinetics

Absorption

In healthy volunteers, valsartan peak plasma concentration is reached 2 to 4 hours after dosing. Valsartan shows bi-exponential decay kinetics following intravenous administration, with an average elimination half-life of about 6 hours. Absolute bioavailability for Diovan is about 25% (range 10% to 35%). The bioavailability of the suspension [see Dosage and Administration (2.2)] is 1.6 times as great as with the tablet. AUC and Cmax values of valsartan increase approximately linearly with increasing dose over the clinical dosing range (80 mg to 320 mg). Valsartan does not accumulate appreciably in plasma following repeated administration of 200 mg once daily.

In heart failure patients, the average time to peak plasma concentration and elimination half-life of valsartan are similar to those observed in healthy volunteers. The average accumulation factor is about 1.7 in heart failure patients following repeated administration of 160 mg twice daily. AUC and Cmax values of valsartan increase linearly and are almost proportional with increasing dose from 40 mg to 160 mg twice a day.

Effect of Food

With the tablet, food decreases the exposure (as measured by AUC) to valsartan by about 40% and peak plasma concentration (Cmax) by about 50%. Diovan can be administered with or without food.

Distribution:

The steady state volume of distribution of valsartan after intravenous administration is small (17 L), indicating that valsartan does not distribute into tissues extensively. Valsartan is highly bound to serum proteins (95%), mainly serum albumin.

Metabolism:

The primary metabolite, accounting for about 9% of dose, is valeryl 4-hydroxy valsartan. In vitro metabolism studies involving recombinant CYP 450 enzymes indicated that the CYP 2C9 isoenzyme is responsible for the formation of valeryl-4-hydroxy valsartan. Valsartan does not inhibit CYP 450 isozymes at clinically relevant concentrations. CYP 450 mediated drug interaction between valsartan and coadministered drugs are unlikely because of the low extent of metabolism.

Excretion

Valsartan, when administered as an oral solution, is primarily recovered in feces (about 83% of dose) and urine (about 13% of dose). The recovery is mainly as unchanged drug, with only about 20% of dose recovered as metabolites.

Following intravenous administration, plasma clearance of valsartan is about 2 L/h and its renal clearance is 0.62 L/h (about 30% of total clearance).

The apparent clearance of valsartan following oral administration is approximately 4.5 L/h in heart failure patients. Age does not affect the apparent clearance in heart failure patients.

Specific Populations:

Geriatric: Exposure (measured by AUC) to valsartan is higher by 70% and the half-life is longer by 35% in the elderly than in the young [see Use in Specific Populations (8.5)].

Pediatric: In a study of pediatric hypertensive patients (n = 26, 1 to 16 years of age) given single doses of a suspension of Diovan (mean: 0.9 mg/kg to 2 mg/kg), the clearance (L/h/kg) of valsartan for children was similar to that of adults receiving the same formulation. Valsartan pharmacokinetics have not been investigated in pediatric patients less than 1 year of age.

Gender: Pharmacokinetics of valsartan does not differ significantly between males and females.

Renal Insufficiency: There is no apparent correlation between renal function (measured by creatinine clearance) and exposure (measured by AUC) to valsartan in patients with different degrees of renal impairment (down to creatinine clearance of 10 mL/min). Valsartan is not removed from the plasma by hemodialysis [see Use in Specific Populations (8.6)].

Hepatic Insufficiency: On average, patients with mild-to-moderate chronic liver disease have twice the exposure (measured by AUC values) to valsartan of healthy volunteers (matched by age, sex, and weight) [see Use in Specific Populations (8.7)].

Drug Interaction Studies

No clinically significant pharmacokinetic interactions were observed when Diovan (valsartan) was coadministered with amlodipine, atenolol, cimetidine, digoxin, furosemide, glyburide, hydrochlorothiazide, or indomethacin. The valsartan-atenolol combination was more antihypertensive than either component, but it did not lower the heart rate more than atenolol alone.

Coadministration of valsartan and warfarin did not change the pharmacokinetics of valsartan or the time-course of the anticoagulant properties of warfarin.

Transporters: The results from an in vitro study with human liver tissue indicate that valsartan is a substrate of the hepatic uptake transporter OATP1B1 and the hepatic efflux transporter MRP2. Coadministration of inhibitors of the uptake transporter (rifampin, cyclosporine) or efflux transporter (ritonavir) may increase the systemic exposure to valsartan.

13 NONCLINICAL TOXICOLOGY

13.1 Carcinogenesis, Mutagenesis, Impairment of Fertility

There was no evidence of carcinogenicity when valsartan was administered in the diet to mice and rats for up to 2 years at doses up to 160 mg/kg/day and 200 mg/kg/day, respectively. These doses in mice and rats are about 2.6 and 6 times, respectively, the MRHD on a mg/m^2 basis (Calculations assume an oral dose of 320 mg/day and a 60-kg patient).

Mutagenicity assays did not reveal any valsartan-related effects at either the gene or chromosome level. These assays included bacterial mutagenicity tests with Salmonella (Ames) and E coli; a gene mutation test with Chinese hamster V79 cells; a cytogenetic test with Chinese hamster ovary cells; and a rat micronucleus test.

Valsartan had no adverse effects on the reproductive performance of male or female rats at oral doses up to 200 mg/kg/day. This dose is 6 times the MRHD on a mg/m^2 basis (Calculations assume an oral dose of 320 mg/day and a 60-kg patient).

13.2 Animal Toxicology and/or Pharmacology

Daily oral dosing of neonatal/juvenile rats with valsartan at doses as low as 1 mg/kg/day (about 10% of the maximum recommended pediatric dose on a mg/m^2 basis) from postnatal day 7 to postnatal day 70 produced persistent, irreversible kidney damage. These kidney effects in neonatal rats represent expected exaggerated pharmacological effects that are observed if rats are treated during the first 13 days of life. This period coincides with 36 weeks of gestation in humans, which could occasionally extend up to 44 weeks after conception in humans. In humans, nephrogenesis is thought to be complete around birth; however, maturation of other aspects of kidney function (such as glomerular filtration and tubular function) may continue until approximately 2 years of age. It is unknown whether post-natal use of valsartan before maturation of renal function is complete has long-term deleterious effects on the kidney [see Use in Specific Populations (8.4)].

14 CLINICAL STUDIES

14.1 Hypertension

Adult Hypertension

The antihypertensive effects of Diovan (valsartan) were demonstrated principally in 7 placebo-controlled, 4- to 12-week trials (1 in patients over 65 years) of dosages from 10 mg/day to 320 mg/day in patients with baseline diastolic blood pressures of 95-115 mmHg. The studies allowed comparison of once-daily and twice-daily regimens of 160 mg/day; comparison of peak and trough effects; comparison (in pooled data) of response by gender, age, and race; and evaluation of incremental effects of hydrochlorothiazide.

Administration of valsartan to patients with essential hypertension results in a significant reduction of sitting, supine, and standing systolic and diastolic blood pressure, usually with little or no orthostatic change.

In most patients, after administration of a single oral dose, onset of antihypertensive activity occurs at approximately 2 hours, and maximum reduction of blood pressure is achieved within 6 hours. The antihypertensive effect persists for 24 hours after dosing, but there is a decrease from peak effect at lower doses (40 mg) presumably reflecting loss of inhibition of angiotensin II. At higher doses, however (160 mg), there is little difference in peak and trough effect. During repeated dosing, the reduction in blood pressure with any dose is substantially present within 2 weeks, and maximal reduction is generally attained after 4 weeks. In long-term follow-up studies (without placebo control), the effect of valsartan appeared to be maintained for up to 2 years. The antihypertensive effect is independent of age, gender or race. The latter finding regarding race is based on pooled data and should be viewed with caution, because antihypertensive drugs that affect the renin-angiotensin system (that is, ACE inhibitors and angiotensin-II blockers) have generally been found to be less effective in low-renin hypertensives (frequently blacks) than in high-renin hypertensives (frequently whites). In pooled, randomized, controlled trials of Diovan that included a total of 140 blacks and 830 whites, valsartan and an ACE-inhibitor control were generally at least as effective in blacks as whites. The explanation for this difference from previous findings is unclear.

Abrupt withdrawal of valsartan has not been associated with a rapid increase in blood pressure.

The blood pressure-lowering effect of valsartan and thiazide-type diuretics are approximately additive.

The 7 studies of valsartan monotherapy included over 2000 patients randomized to various doses of valsartan and about 800 patients randomized to placebo. Doses below 80 mg were not consistently distinguished from those of placebo at trough, but doses of 80 mg, 160 mg and 320 mg produced dose-related decreases in systolic and diastolic blood pressure, with the difference from placebo of approximately 6-9/3-5 mmHg at 80 mg to 160 mg and 9/6 mmHg at 320 mg. In a controlled trial the addition of HCTZ to valsartan 80 mg resulted in additional lowering of systolic and diastolic blood pressure by approximately 6/3 and 12/5 mmHg for 12.5 and 25 mg of HCTZ, respectively, compared to valsartan 80 mg alone.

Patients with an inadequate response to 80 mg once daily were titrated to either 160 mg once daily or 80 mg twice daily, which resulted in a similar response in both groups.

In controlled trials, the antihypertensive effect of once-daily valsartan 80 mg was similar to that of once-daily enalapril 20 mg or once-daily lisinopril 10 mg.

There are no trials of Diovan demonstrating reductions in cardiovascular risk in patients with hypertension, but at least one pharmacologically similar drug has demonstrated such benefits.

There was essentially no change in heart rate in valsartan-treated patients in controlled trials.

Pediatric Hypertension

Children Between 1 to Less Than 6 Years of Age

The antihypertensive effect of valsartan in 290 children aged between 1 to less than 6 years of age has been evaluated in three randomized, double-blind clinical studies. In the first study in 90 patients, patients who weighed less than 18 kg received 5 mg, 20 mg or 40 mg of valsartan daily (low, medium and high doses), and patients who weighed greater than or equal to 18 kg received 10 mg, 40 mg, and 80 mg of valsartan daily (low, medium and high doses). At the end of 2 weeks, the three dose levels of valsartan (low, medium and high) reduced systolic blood pressure from the baseline by 8.4, 8.3, and 8.6 mmHg, respectively, but a dose response could not be demonstrated. In the second study of 74 patients, higher doses (1 mg/kg and 4 mg/kg daily) of valsartan were associated with numerically greater blood pressure reductions than the lowest dose (0.25 mg/kg) at the end of 6-weeks treatment. The third study was a 6-weeks, randomized double-blind study to evaluate the dose response of valsartan in 126 children 1 to 5 years of age with hypertension, with or without chronic kidney disease (CKD) randomized to receive either valsartan 0.25 mg/kg or 4 mg/kg daily. At the end of 6 weeks, dose dependent reductions in mean systolic blood pressure (MSBP) were observed. The reduction in MSBP was 8.5 mmHg with valsartan 4 mg/kg and 4.1 mmHg with valsartan 0.25 mg/kg. Similarly, the CKD subgroup showed reductions in MSBP with valsartan 4 mg/kg compared to 0.25 mg/kg (9.2 mmHg vs 1.2 mmHg).

Children Between 6 to 16 Years of Age

In a clinical study involving 261 hypertensive pediatric patients 6 to 16 years of age, patients who weighed less than 35 kg received 10 mg, 40 mg or 80 mg of valsartan daily (low, medium and high doses), and patients who weighed greater than or equal to 35 kg received 20 mg, 80 mg, and 160 mg of valsartan daily (low, medium and high doses). Renal and urinary disorders, and essential hypertension with or without obesity were the most common underlying causes of hypertension in children enrolled in this study. At the end of 2 weeks, valsartan reduced both systolic and diastolic blood pressure in a dose-dependent manner. Overall, the three dose levels of valsartan (low, medium and high) significantly reduced systolic blood pressure by 8, 10, and 12 mm Hg from the baseline, respectively. Patients were re-randomized to either continue receiving the same dose of valsartan or were switched to placebo. In patients who continued to receive the medium and high doses of valsartan, systolic blood pressure at trough was 4 and 7 mm Hg lower than patients who received the placebo treatment. In patients receiving the low dose of valsartan, systolic blood pressure at trough was similar to that of patients who received the placebo treatment. Overall, the dose-dependent antihypertensive effect of valsartan was consistent across all the demographic subgroups.

14.2 Heart Failure

The Valsartan Heart Failure Trial (Val-HeFT) was a multinational, double-blind study in which 5010 patients with NYHA class II (62%) to IV (2%) heart failure and LVEF less than 40%, on baseline therapy chosen by their physicians, were randomized to placebo or valsartan (titrated from 40 mg twice daily to the highest tolerated dose or 160 mg twice daily) and followed for a mean of about 2 years. Although Val-HeFT’s primary goal was to examine the effect of valsartan when added to an ACE inhibitor, about 7% were not receiving an ACE inhibitor. Other background therapy included diuretics (86%), digoxin (67%), and beta-blockers (36%). The population studied was 80% male, 46% 65 years or older and 89% Caucasian. At the end of the trial, patients in the valsartan group had a blood pressure that was 4 mmHg systolic and 2 mmHg diastolic lower than the placebo group. There were two primary end points, both assessed as time to first event: all-cause mortality and heart failure morbidity, the latter defined as all-cause mortality, sudden death with resuscitation, hospitalization for heart failure, and the need for intravenous inotropic or vasodilatory drugs for at least 4 hours. These results are summarized in the following table.

 | Placebo | Valsartan | Hazard Ratio | Nominal
 | (N = 2499) | (N = 2511) | (95% CI*) | p-value
All-cause mortality | 484 | 495 | 1.02 | 0.8
 | (19.4%) | (19.7%) | (0.90-1.15)
HF morbidity | 801 | 723 | 0.87 | 0.009
 | (32.1%) | (28.8%) | (0.79-0.97)
* CI = Confidence Interval

Although the overall morbidity result favored valsartan, this result was largely driven by the 7% of patients not receiving an ACE inhibitor, as shown in the following table.

 | Without ACE Inhibitor |  | With ACE Inhibitor
 | Placebo | Valsartan | Placebo | Valsartan
 | (N = 181) | (N = 185) | (N = 2318) | (N = 2326)
Events (%) | 77 (42.5%) | 46 (24.9%) | 724 (31.2%) | 677 (29.1%)
Hazard ratio (95% CI) | 0.51 (0.35, 0.73) |  | 0.92 (0.82, 1.02)
p-value | 0.0002 |  | 0.0965

The modest favorable trend in the group receiving an ACE inhibitor was largely driven by the patients receiving less than the recommended dose of ACE inhibitor. Thus, there is little evidence of further clinical benefit when valsartan is added to an adequate dose of ACE inhibitor.

Secondary end points in the subgroup not receiving ACE inhibitors were as follows.

 | Placebo | Valsartan | Hazard Ratio
 | (N = 181) | (N = 185) | (95% CI)
Components of HF morbidity
All-cause mortality | 49 (27.1%) | 32 (17.3%) | 0.59 (0.37, 0.91)
Sudden death with resuscitation | 2 (1.1%) | 1 (0.5%) | 0.47 (0.04, 5.20)
CHF therapy | 1 (0.6%) | 0 (0.0%) | –
CHF hospitalization | 48 (26.5%) | 24 (13.0%) | 0.43 (0.27, 0.71)
Cardiovascular mortality | 40 (22.1%) | 29 (15.7%) | 0.65 (0.40, 1.05)
Non-fatal morbidity | 49 (27.1%) | 24 (13.0%) | 0.42 (0.26, 0.69)

In patients not receiving an ACE inhibitor, valsartan-treated patients had an increase in ejection fraction and reduction in left ventricular internal diastolic diameter (LVIDD).

Effects were generally consistent across subgroups defined by age and gender for the population of patients not receiving an ACE inhibitor. The number of black patients was small and does not permit a meaningful assessment in this subset of patients.

14.3 Post-Myocardial Infarction

The VALsartan In Acute myocardial iNfarcTion trial (VALIANT) was a randomized, controlled, multinational, double-blind study in 14703 patients with acute myocardial infarction and either heart failure (signs, symptoms or radiological evidence) or left ventricular systolic dysfunction (ejection fraction ≤ 40% by radionuclide ventriculography or ≤ 35% by echocardiography or ventricular contrast angiography). Patients were randomized within 12 hours to 10 days after the onset of myocardial infarction symptoms to one of three treatment groups: valsartan (titrated from 20 mg or 40 mg twice daily to the highest tolerated dose up to a maximum of 160 mg twice daily), the ACE inhibitor, captopril (titrated from 6.25 mg three times daily to the highest tolerated dose up to a maximum of 50 mg three times daily), or the combination of valsartan plus captopril. In the combination group, the dose of valsartan was titrated from 20 mg twice daily to the highest tolerated dose up to a maximum of 80 mg twice daily; the dose of captopril was the same as for monotherapy. The population studied was 69% male, 94% Caucasian, and 53% were 65 years of age or older. Baseline therapy included aspirin (91%), beta-blockers (70%), ACE inhibitors (40%), thrombolytics (35%) and statins (34%). The mean treatment duration was 2 years. The mean daily dose of Diovan in the monotherapy group was 217 mg.

The primary endpoint was time to all-cause mortality. Secondary endpoints included (1) time to cardiovascular (CV) mortality, and (2) time to the first event of cardiovascular mortality, reinfarction, or hospitalization for heart failure. The results are summarized in the following table.

 | Valsartan vs. Captopril (N = 4909) (N = 4909) |  |  | Valsartan + Captopril vs. Captopril (N = 4885) (N = 4909)
 | No. of Deaths Valsartan/Captopril | Hazard Ratio CI | p-value | No. of Deaths Comb/Captopril | Hazard Ratio CI | p-value
All-cause mortality | 979 (19.9%) /958 (19.5%) | 1.001 (0.902, 1.111) | 0.98 | 941 (19.3%) /958 (19.5%) | 0.984 (0.886, 1.093) | 0.73
CV mortality | 827 (16.8%) /830 (16.9%) | 0.976 (0.875, 1.090)
CV mortality, hospitalization for HF, and recurrent non-fatal MI | 1529 (31.1%) /1567 (31.9%) | 0.955 (0.881, 1.035)

There was no difference in overall mortality among the three treatment groups. There was thus no evidence that combining the ACE inhibitor captopril and the angiotensin II blocker valsartan was of value.

The data were assessed to see whether the effectiveness of valsartan could be demonstrated by showing in a non-inferiority analysis that it preserved a fraction of the effect of captopril, a drug with a demonstrated survival effect in this setting. A conservative estimate of the effect of captopril (based on a pooled analysis of 3 post-infarction studies of captopril and 2 other ACE inhibitors) was a 14% to 16% reduction in mortality compared to placebo. Valsartan would be considered effective if it preserved a meaningful fraction of that effect and unequivocally preserved some of that effect. As shown in the table, the upper bound of the CI for the hazard ratio (valsartan/captopril) for overall or CV mortality is 1.09 to 1.11, a difference of about 9% to 11%, thus making it unlikely that valsartan has less than about half of the estimated effect of captopril and clearly demonstrating an effect of valsartan. The other secondary endpoints were consistent with this conclusion.

Effects on Mortality Amongst Subgroups in VALIANT

There were no clear differences in all-cause mortality based on age, gender, race, or baseline therapies, as shown in the figure above.

16 HOW SUPPLIED/STORAGE AND HANDLING

Diovan (valsartan) is available as tablets containing valsartan 40 mg, 80 mg, 160 mg, or 320 mg. All strengths are packaged in bottles as described below.

Tablet | Color | Shape/coating | Functional Scoring | Deboss |  | NDC 0078-####-##
 |  |  |  | Side 1 | Side 2 | Bottle of
 |  |  |  |  |  | 30 | 90
40 mg | Yellow | ovaloid film-coated tablets with beveled edges, slightly convex | Yes | NVR | DO | 0423-15 | –
40 mg | Yellow | ovaloid film-coated tablets with beveled edges, slightly convex | Yes | NVR | DO | 0423-15 | –
80 mg | Pale red | almond shaped film-coated tablets with beveled edges | No | NVR | DV | – | 0358-34
80 mg | Pale red | round film-coated tablets with beveled edges | No | NVR | DV | – | 1245-34
160 mg | Grey-orange | almond shaped film-coated tablets with beveled edges | No | NVR | DX | – | 0359-34
160 mg | Grey-orange | ovaloid film-coated tablets, slightly convex | No | NVR | DX | – | 1252-34
320 mg | Dark grey-violet | almond shaped film-coated tablets with beveled edges | No | NVR | DXL | – | 0360-34
320 mg | Dark grey-violet | ovaloid film-coated tablets with beveled edges, slightly convex, | No | NVR | DC | – | 1259-34

Store at 20°C to 25°C (68°F to 77°F); excursions permitted between 15°C and 30°C (59°F and 86°F) [see USP Controlled Room Temperature].

Protect from moisture.

Dispense in tight container (USP).

17 PATIENT COUNSELING INFORMATION

Advise the patient to read the FDA-approved patient labeling (Patient Information).

Pregnancy: Advise female patients of childbearing age about the consequences of exposure to Diovan during pregnancy. Discuss treatment options with women planning to become pregnant. Ask patients to report pregnancies to their healthcare provider as soon as possible [see Warnings and Precautions (5.1), Use in Specific Populations (8.1)].

Lactation: Advise women not to breastfeed during treatment with Diovan [see Use in Specific Populations (8.2)].

Symptomatic Hypotension: Advise patients that lightheadedness can occur, especially during the first days of therapy, and that it should be reported to their healthcare provider. Tell patients that if syncope occurs to discontinue Diovan until the physician has been consulted. Caution all patients that inadequate fluid intake, excessive perspiration, diarrhea, or vomiting can lead to an excessive fall in blood pressure, with the same consequences of lightheadedness and possible syncope [see Warnings and Precautions (5.2)].

Hyperkalemia: Advise patients not to use salt substitutes without consulting their healthcare provider [see Drug Interactions (7.1)].

Distributed by:
Novartis Pharmaceuticals Corporation
East Hanover, New Jersey 07936
© Novartis

T2025-42

PATIENT INFORMATION
DIOVAN® (DYE-o-van)
(valsartan) tablets

What is the most important information I should know about DIOVAN?
DIOVAN can cause harm or death to an unborn baby.

- Talk to your healthcare provider about other ways to lower your blood pressure if you plan to become pregnant.
- If you become pregnant during treatment with DIOVAN, stop taking DIOVAN and tell your healthcare provider right away.

What is DIOVAN?
DIOVAN is a prescription medicine used in:

- adults and children 1 year of age and older to lower high blood pressure (hypertension). DIOVAN may be used alone or in combination with other blood pressure medicines.
- adults to treat heart failure. DIOVAN may help decrease your need for hospitalization that happens with heart failure.
- adults with certain types of heart failure, to increase the chance of living longer after a heart attack (myocardial infarction).

DIOVAN should not be used to treat high blood pressure in children less than 1 year of age.
It is not known if DIOVAN is safe and effective in children with certain kidney problems.

Do not take DIOVAN if you:

- are allergic to any of the ingredients in DIOVAN. See the end of this leaflet for a complete list of ingredients in DIOVAN.
- have diabetes and are also taking aliskiren. Talk to your healthcare provider if you are not sure.

Before taking DIOVAN, tell your healthcare provider about all of your medical conditions including, if you:

- have heart problems
- have kidney problems
- are pregnant or plan to become pregnant. See “What is the most important information I should know about DIOVAN?
- are breastfeeding or plan to breastfeed. It is not known if DIOVAN passes into your breast milk. You should not breastfeed during treatment with DIOVAN. Talk with your healthcare provider about the best way to feed your baby during your treatment with DIOVAN.

Tell your healthcare provider about all the medicines you take including prescription and over- the-counter medicines, vitamins and herbal supplements. DIOVAN may affect the way other medicines work.
Especially tell your healthcare provider if you take:

- other medicines for high blood pressure or a heart problem
- water pills (also called “diuretics”)
- potassium-containing medicines, potassium supplements or salt substitutes containing potassium. Your healthcare provider may check the amount of potassium in your blood regularly.
- nonsteroidal anti-inflammatory drugs (NSAIDs)
- Lithium. Your healthcare provider will check the amount of lithium in your blood regularly.

Know the medicines you take. Keep a list of your medicines with you to show to your healthcare provider and pharmacist when a new medicine is prescribed. Talk to your healthcare provider or pharmacist before you start taking any new medicine.

How should I take DIOVAN?

- Take DIOVAN exactly as prescribed by your healthcare provider.
- For treatment of high blood pressure, take DIOVAN 1 time each day
- For children: Your pharmacist will mix DIOVAN as a liquid suspension for your child, if:
  - your child is 1 to 5 years of age, or
  - your child is older than 5 years of age and cannot swallow tablets, or
  - if tablets are not available in the prescribed strength needed for your child
- If your child switches between taking the tablet and the suspension, your healthcare provider will adjust the dose as needed.
  - Shake the bottle of suspension well for at least 10 seconds before pouring the dose of medicine to give to your child.
- For adults with heart failure or who have had a heart attack, take DIOVAN 2 times each day. Your healthcare provider may start you on a low dose of DIOVAN and may increase the dose during your treatment.
- DIOVAN can be taken with or without food.
- If you miss a dose, take it as soon as you remember. If it is close to your next dose, do not take the missed dose. Take the next dose at your regular time.

If you take too much DIOVAN, call your healthcare provider, or go to the nearest hospital emergency room.

What are the possible side effects of DIOVAN?

- DIOVAN can cause serious side effects, including: See “What is the most important information I should know about DIOVAN?”
- Low blood pressure (hypotension). Low blood pressure can happen with DIOVAN, especially when you first start taking it and can cause you to feel lightheaded. Feeling lightheaded is most likely to happen if you:

○ take water pills
○ are on a low-salt diet
○ get dialysis treatments
○ do not drink enough liquids

○ are dehydrated (decreased body fluids) due to vomiting and diarrhea
○ you sweat excessively
○ have heart problems

Lie down, if you feel lightheaded, dizzy or faint. Call your healthcare provider right away.

- Kidney problems. Kidney problems may get worse in people that already have kidney disease or heart problems. Your doctor may do blood tests to check for this.
- Increased potassium in your blood. Some people may develop increased potassium in the blood during treatment with DIOVAN. Your doctor may do a blood test to check your potassium levels as needed.

The most common side effects of DIOVAN when used to treat people with high blood pressure include:

- headache
- dizziness
- flu symptoms
- tiredness
- stomach (abdominal) pain

The most common side effects of DIOVAN when used to treat people with heart failure include:

- dizziness
- low blood pressure
- diarrhea
- joint and back pain
- tiredness
- high blood potassium

The most common side effects of DIOVAN when used to treat people after a heart attack that cause them to stop taking DIOVAN include:

- low blood pressure
- cough
- high blood creatinine (decreased kidney function)

You should not stop taking DIOVAN without talking to your healthcare provider. These are not all of the possible side effects of DIOVAN. For more information, ask your healthcare provider or pharmacist.
Call your doctor for medical advice about side effects. You may report side effects to FDA at 1-800-FDA-1088.

How should I store DIOVAN?

- Store DIOVAN tablets at room temperature between 68ºF to 77ºF (20ºC to 25 ºC).
- Keep DIOVAN tablets container tightly closed and in a dry place to protect from moisture.
- DIOVAN suspension is provided in a glass bottle with a child-resistant screw-cap closure.
- Store bottles of DIOVAN suspension at room temperature less than 86ºF (30ºC) for up to 30 days, or refrigerate between 35ºF to 46ºF (2ºC to 8ºC) for up to 75 days.

Keep DIOVAN and all medicines out of the reach of children.

General information about the safe and effective use of DIOVAN.
Medicines are sometimes prescribed for purposes other than those listed in a Patient Information Leaflet. Do not use DIOVAN for a condition for which it was not prescribed. Do not give DIOVAN to other people, even if they have the same symptoms you have. It may harm them.
You can ask your healthcare provider or pharmacist for information about DIOVAN that is written for health professionals.

What are the ingredients in DIOVAN?
Active ingredient: valsartan
Inactive ingredients: colloidal silicon dioxide, crospovidone, hydroxypropyl methylcellulose, iron oxides (yellow, black and/or red), magnesium stearate, microcrystalline cellulose, polyethylene glycol 8000, and titanium dioxide
Distributed by:
Novartis Pharmaceuticals Corporation
East Hanover, NJ 07936
© Novartis
For more information, go to www.DIOVAN.com or call 1-888-669-6682.

This Patient Information has been approved by the U.S. Food and Drug Administration.

Revised: December 2024

T2024-84

PRINCIPAL DISPLAY PANEL

NDC 0078-0423-15

Diovan®
valsartan

40 mg

30 Scored Tablets

Rx only

NOVARTIS

PRINCIPAL DISPLAY PANEL

NDC 0078-0358-34

Diovan®
valsartan

80 mg

90 Tablets

Rx only

NOVARTIS

PRINCIPAL DISPLAY PANEL

NDC 0078-1245-34

Diovan®
valsartan

80 mg

90 Tablets

Rx only

NOVARTIS

PRINCIPAL DISPLAY PANEL

NDC 0078-0359-34

Diovan®
valsartan

160 mg

90 Tablets

Rx only

NOVARTIS

PRINCIPAL DISPLAY PANEL

NDC 0078-1252-34

Diovan®
valsartan

160 mg

90 Tablets

Rx only

NOVARTIS

PRINCIPAL DISPLAY PANEL

NDC 0078-0360-34

Diovan®
valsartan

320 mg

90 Tablets

Rx only

NOVARTIS

PRINCIPAL DISPLAY PANEL

NDC 0078-1259-34

Diovan®
valsartan

320 mg

90 Tablets

Rx only

NOVARTIS